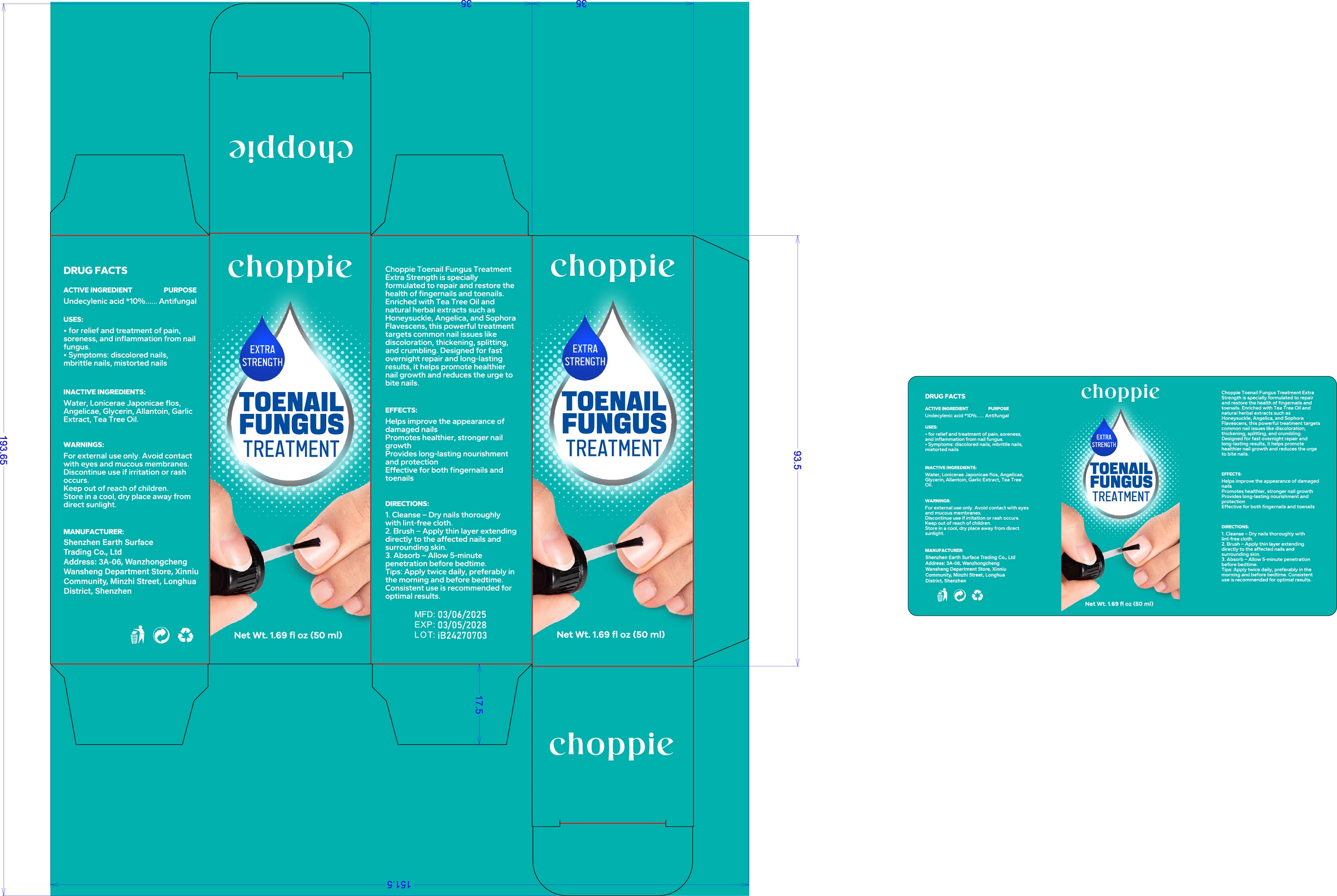 DRUG LABEL: Toenail Fungus Liquid
NDC: 85636-001 | Form: LIQUID
Manufacturer: Shenzhen Earth Surface Trading Co., Ltd.
Category: otc | Type: HUMAN OTC DRUG LABEL
Date: 20250527

ACTIVE INGREDIENTS: UNDECYLENIC ACID 100 mg/1 mL; EUCALYPTOL 1000 mg/1 mL
INACTIVE INGREDIENTS: WATER

Active ingredients

Salicylic Acid

PURPOSE

Anti-fungal

Uses

Uses for relief and treatment of pain,soreness, and inflammation from nail fungus.
Symptoms: ■ discolored nails ■ brittle nails ■ distorted nails

Warnings

For external use only, Some individuals may be sensitive to essential oils.
Begin with a small drop to determine if product causes any irritation. Discontinue use if any irritation occurs.
Stop use and consult a doctor if condition worsens, Not for use on children under the age of 2 without physician direction.

Stop use and ask a doctor if

rash occur

Do not use

on damaged or broken skik

Keep out of reach of children.

If swallwed, get medical help or contact a Poison Control Center right away.

inactive ingredients

Water

DOSAGE & ADMINISTRATION

shake well before use.Wash and thoroughly dry the affectedarea. Apply 1-2 drops and gently rubinto affected area three times per day.